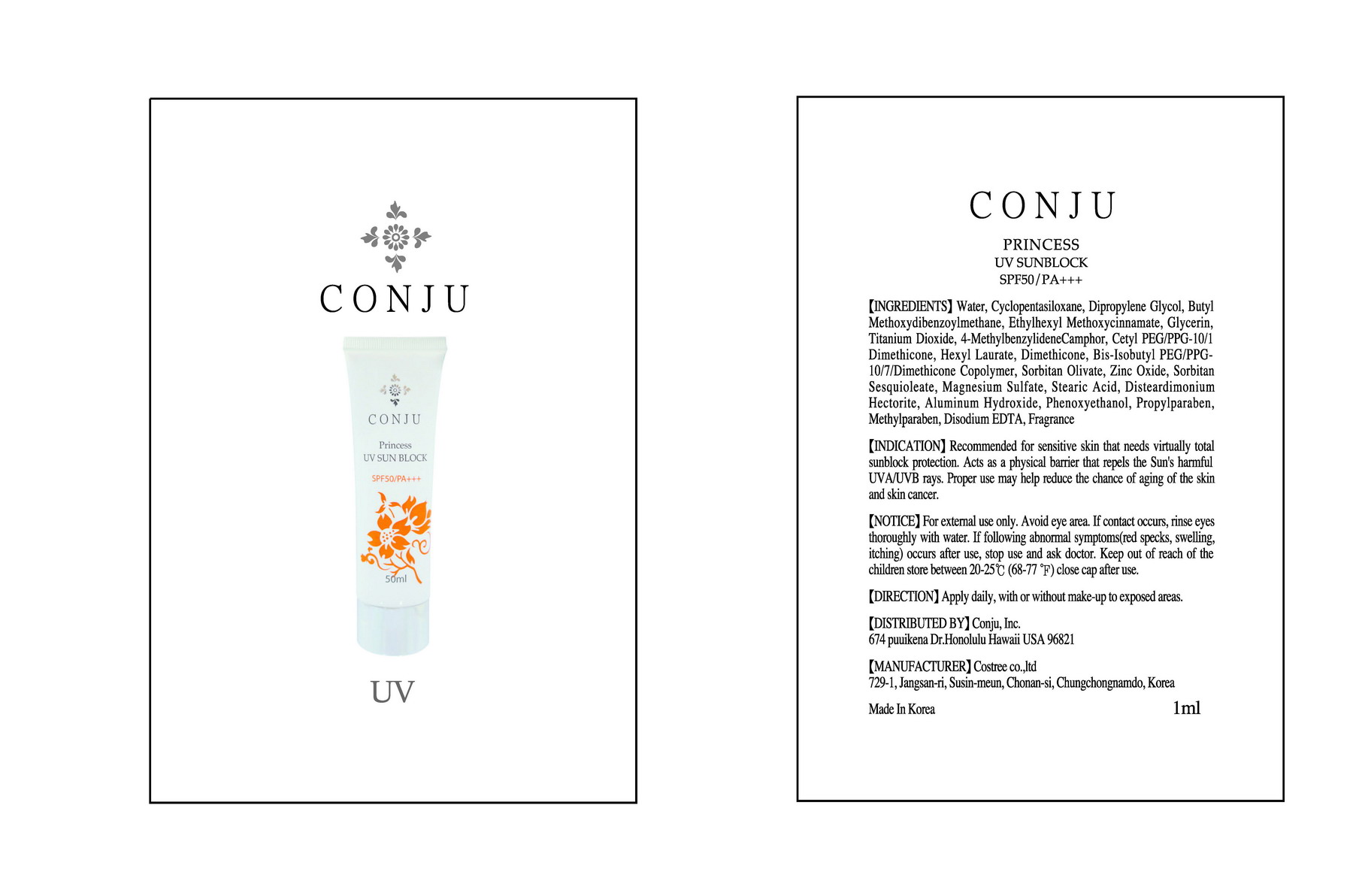 DRUG LABEL: Conju Princess UV Sun Block
NDC: 59915-4001 | Form: CREAM
Manufacturer: Conju Inc
Category: otc | Type: HUMAN OTC DRUG LABEL
Date: 20101230

ACTIVE INGREDIENTS: OCTINOXATE 0.075 mL/1 mL; ENZACAMENE 0.05 mL/1 mL; TITANIUM DIOXIDE 0.0249 mL/1 mL; AVOBENZONE 0.03 mL/1 mL; ZINC OXIDE 0.01 mL/1 mL
INACTIVE INGREDIENTS: WATER; CYCLOMETHICONE 5; DIPROPYLENE GLYCOL; GLYCERIN; DIMETHICONE; HEXYL LAURATE; SORBITAN OLIVATE; SORBITAN SESQUIOLEATE; MAGNESIUM SULFATE, UNSPECIFIED; STEARIC ACID; HECTORITE; ALUMINUM HYDROXIDE; PHENOXYETHANOL; PROPYLPARABEN; METHYLPARABEN; EDETATE DISODIUM

Drug Facts

ACTIVE INGREDIENT

active ingredients: Ethylhexyl methoxycinnamate, 4-methylbenzylidene camphor, butyl methoxydibenzoylmethane, titanium dioxide, zinc oxide

inactive ingredient: water, cyclopentasiloxane, dipropylene glycol, glycerin, dimethicone, hexyl laurate, sorbitan olivate, sorbitan sesquioleate, magnesium sulfate, stearic acid, hectorite, aluminum hydroxide, phenoxyethanol, propylparaben, methylparaben, disodium EDTA, fragrance

PURPOSE

Recommended for sensitive skin that needs virtually total sunblock protection

keep out of reach of the children

INDICATIONS AND USAGE

Apply daily, with or without make-up to exposed areas

WARNINGS

Avoid eye area. If contact occurs, rinse eyes thoroughly with water.
If following abnormal symptoms (red specks, swelling, itching) occurs after use, stop use and ask doctor.

DOSAGE AND ADMINISTRATION

Apply daily, with or without make-up to exposed areas